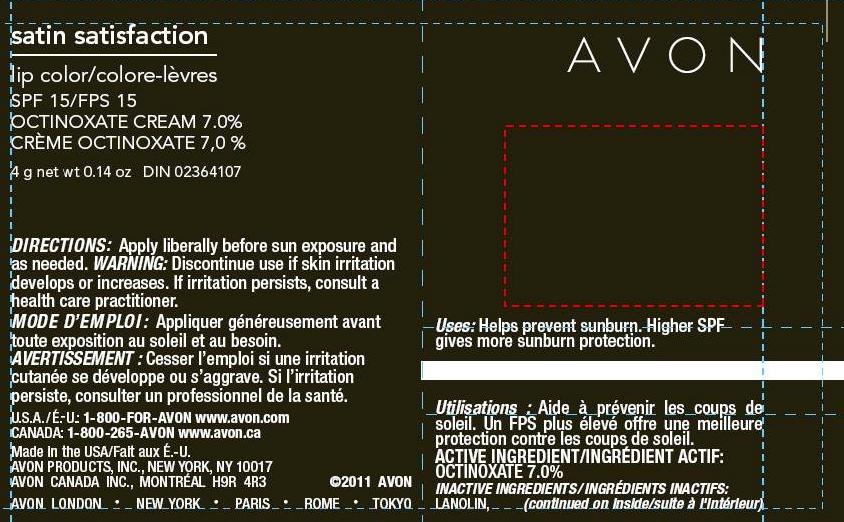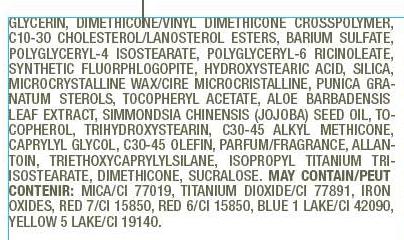 DRUG LABEL: Satin Satisfaction
NDC: 10096-0261 | Form: LIPSTICK
Manufacturer: Avon Products, Inc.
Category: otc | Type: HUMAN OTC DRUG LABEL
Date: 20110425

ACTIVE INGREDIENTS: OCTINOXATE 0.28 g/4 g

DOSAGE AND ADMINISTRATION

DIRECTIONS: Apply liberally before sun exposure and
as needed.

WARNINGS

WARNING: Discontinue use if skin irritation
develops or increases. If irritation persists, consult a
health care practitioner.

INDICATIONS AND USAGE

Uses: Helps prevent sunburn. Higher SPF
gives more sunburn protection.

ACTIVE INGREDIENT/INGRÉDIENT ACTIF:
OCTINOXATE 7.0%

INACTIVE INGREDIENTS/INGRÉDIENTS INACTIFS:
LANOLIN, GLYCERIN, DIMETHICONE/VINYL DIMETHICONE CROSSPOLYMER,
C10-30 CHOLESTEROL/LANOSTEROL ESTERS, BARIUM SULFATE,
POLYGLYCERYL-4 ISOSTEARATE, POLYGLYCERYL-6 RICINOLEATE,
SYNTHETIC FLUORPHLOGOPITE, HYDROXYSTEARIC ACID, SILICA,
MICROCRYSTALLINE WAX/CIRE MICROCRISTALLINE, PUNICA GRANATUM
STEROLS, TOCOPHERYL ACETATE, ALOE BARBADENSIS
LEAF EXTRACT, SIMMONDSIA CHINENSIS (JOJOBA) SEED OIL, TOCOPHEROL,
TRIHYDROXYSTEARIN, C30-45 ALKYL METHICONE,
CAPRYLYL GLYCOL, C30-45 OLEFIN, PARFUM/FRAGRANCE, ALLANTOIN,
TRIETHOXYCAPRYLYLSILANE, ISOPROPYL TITANIUM TRIISOSTEARATE,
DIMETHICONE, SUCRALOSE. MAY CONTAIN/PEUT
CONTENIR: MICA/CI 77019, TITANIUM DIOXIDE/CI 77891, IRON
OXIDES, RED 7/CI 15850, RED 6/CI 15850, BLUE 1 LAKE/CI 42090,
YELLOW 5 LAKE/CI 19140.